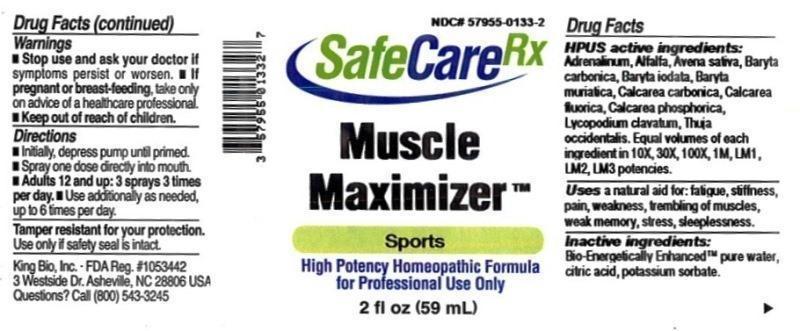 DRUG LABEL: Muscle Maximizer
NDC: 57955-0133 | Form: LIQUID
Manufacturer: King Bio Inc.
Category: homeopathic | Type: HUMAN OTC DRUG LABEL
Date: 20150601

ACTIVE INGREDIENTS: EPINEPHRINE 10 [hp_X]/59 mL; ALFALFA 10 [hp_X]/59 mL; AVENA SATIVA FLOWERING TOP 10 [hp_X]/59 mL; BARIUM CARBONATE 10 [hp_X]/59 mL; BARIUM IODIDE 10 [hp_X]/59 mL; BARIUM CHLORIDE DIHYDRATE 10 [hp_X]/59 mL; OYSTER SHELL CALCIUM CARBONATE, CRUDE 10 [hp_X]/59 mL; CALCIUM FLUORIDE 10 [hp_X]/59 mL; TRIBASIC CALCIUM PHOSPHATE 10 [hp_X]/59 mL; LYCOPODIUM CLAVATUM SPORE 10 [hp_X]/59 mL; THUJA OCCIDENTALIS LEAFY TWIG 10 [hp_X]/59 mL
INACTIVE INGREDIENTS: WATER; ANHYDROUS CITRIC ACID; POTASSIUM SORBATE

Muscle Maximizer™

ACTIVE INGREDIENT

Drug Facts__________________________________________________________________________________________________________

HPUSactive ingredients: Adrenalinum, Alfalfa, Avena sativa, Baryta carbonica, Baryta lodata, Baryta muriatica, Calcarea carbonica, Calcarea fluorica, Calcarea phosphorica, Lycopodium clavatum, Thuja occidentalis. Equal volumes of each ingredient in 10X, 30X, 100X, 1M, LM1, LM2, LM3 potencies.

INDICATIONS AND USAGE

Uses a natural aid for: fatigue, stiffness, pain, weakness, trembling of muscles, weak memory, stress, sleeplessness.

Inactive Ingredients:

Bio-Energetically Enhanced™ pure water, citric acid and potassium sorbate.

Warnings

- Stop use and ask your doctor if symptoms persist or worsen.
- If pregnant or breast-feeding, take only on advice of a healthcare professional.

- Keep out of reach of children.

Directions

- Initially, depress pump until primed.
- Spray one dose directly into mouth.
- Adults 12 and up: 3 sprays 3 times per day.
- Use additionally as needed, up to 6 times per day.

OTHER SAFETY INFORMATION

Tamper resistant for your protection. Use only if safety seal is intact.

PURPOSE

Uses a natural aid for:

- fatigue
- stiffness
- pain
- weakness
- trembling of muscles
- weak memory
- stress
- sleeplessness